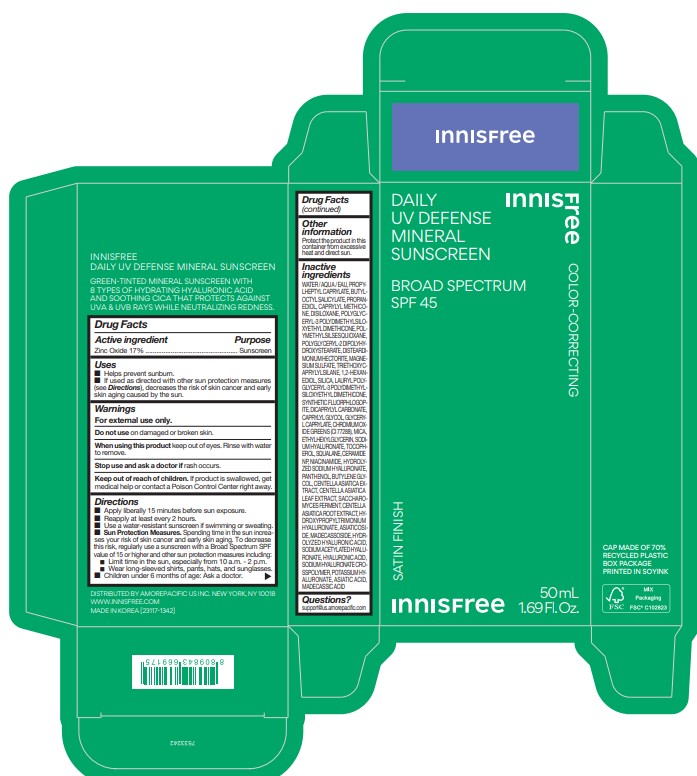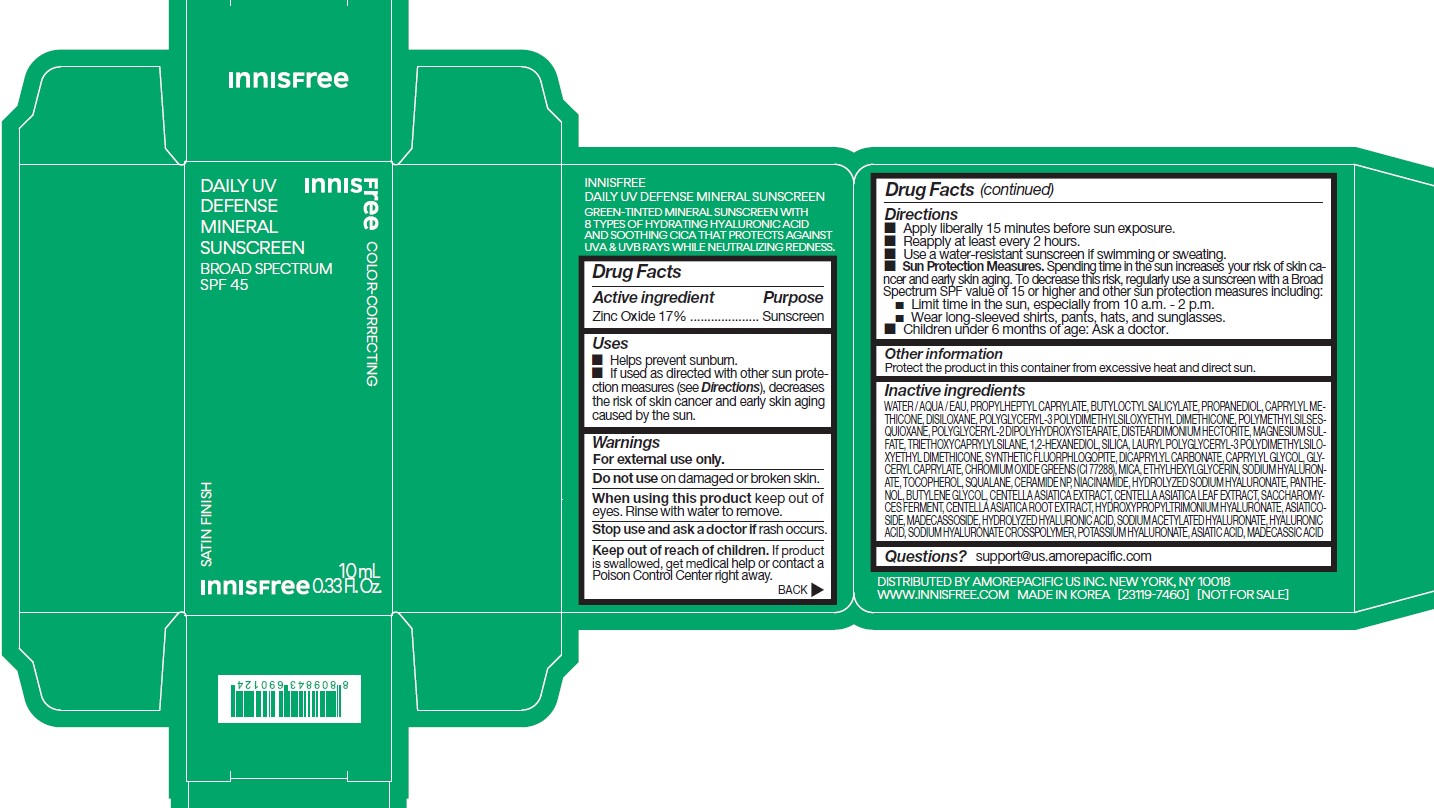 DRUG LABEL: Innisfree Daily UV Defense Mineral Sunscreen
NDC: 71220-087 | Form: LOTION
Manufacturer: Innisfree Corporation
Category: otc | Type: HUMAN OTC DRUG LABEL
Date: 20241104

ACTIVE INGREDIENTS: ZINC OXIDE 8 g/50 mL
INACTIVE INGREDIENTS: CENTELLA ASIATICA ROOT; MADECASSOSIDE; 1,2-HEXANEDIOL; PANTHENOL; PROPYLHEPTYL CAPRYLATE; BUTYLOCTYL SALICYLATE; MAGNESIUM SULFATE, UNSPECIFIED; TRIETHOXYCAPRYLYLSILANE; MAGNESIUM POTASSIUM ALUMINOSILICATE FLUORIDE; DICAPRYLYL CARBONATE; MICA; BUTYLENE GLYCOL; TOCOPHEROL; WATER; POLYGLYCERYL-2 DIPOLYHYDROXYSTEARATE; DISTEARDIMONIUM HECTORITE; GLYCERYL CAPRYLATE; ETHYLHEXYLGLYCERIN; HYALURONATE SODIUM; SQUALANE; CENTELLA ASIATICA LEAF; HYALURONIC ACID; SILICON DIOXIDE; CAPRYLYL GLYCOL; CHROMIC OXIDE; CERAMIDE NP; NIACINAMIDE; SACCHAROMYCES CEREVISIAE; MADECASSIC ACID; SODIUM ACETYLATED HYALURONATE; CENTELLA ASIATICA TRITERPENOIDS; ASIATIC ACID; ASIATICOSIDE; POLYGLYCERYL-3 POLYDIMETHYLSILOXYETHYL DIMETHICONE (4000 MPA.S); POLYMETHYLSILSESQUIOXANE (4.5 MICRONS); CAPRYLYL TRISILOXANE; PROPANEDIOL; HEXAMETHYLDISILOXANE

innisfree Daily UV Defense Mineral Sunscreen

Drug Facts

ACTIVE INGREDIENTS

Zinc Oxide 17%

Purpose

Sunscreen

Uses

- Helps prevent sunburn
- If used as directed with other sun protection measures (see Directions), decreases the risk of skin cancer and early skin aging causes by the sun

Warnings

For external use only

Do not use on damanged or broken skin

When using this product keep out of eyes. Rinse with water to remove.

Stop use and ask a doctor if rash occurs.

Keep out of reach of children. If product is swallowed, get medical help or contact a Poison Control Center right away.

Directions

- Apply liberally 15 minutes before sun exposure.
- Reapply at least every 2 hours.
- Use a water-resistant sunscreen if swimming or sweating.
- Sun Protection Measures. Spending time in the sun increases your risk of skin cancer and early skin aging. To decrease this risk, regularly use a sunscreen with a Broad Spectrum SPF value of 15 or higher and other sun protection measures including :

- Limit time in the sun, especially from 10 a.m. - 2 p.m.

- Wear long-sleeved shirts, pants, hats, and sunglasses.

- Children under 6 months of age : Ask a doctor.

Inactive ingredients

WATER / AQUA / EAU, PROPYLHEPTYL CAPRYLATE, BUTYLOCTYL SALICYLATE, PROPANEDIOL, CAPRYLYL METHICONE, DISILOXANE, POLYGLYCERYL-3 POLYDIMETHYLSILOXYETHYL DIMETHICONE, POLYMETHYLSILSESQUIOXANE, POLYGLYCERYL-2 DIPOLYHYDROXYSTEARATE, DISTEARDIMONIUM HECTORITE, MAGNESIUM SULFATE, TRIETHOXYCAPRYLYLSILANE, 1,2-HEXANEDIOL, SILICA, LAURYL POLYGLYCERYL-3 POLYDIMETHYLSILOXYETHYL DIMETHICONE, SYNTHETIC FLUORPHLOGOPITE, DICAPRYLYL CARBONATE, CAPRYLYL GLYCOL, GLYCERYL CAPRYLATE, CHROMIUM OXIDE GREENS (CI 77288), MICA, ETHYLHEXYLGLYCERIN, SODIUM HYALURONATE, TOCOPHEROL, SQUALANE, CERAMIDE NP, NIACINAMIDE, HYDROLYZED SODIUM HYALURONATE, PANTHENOL, BUTYLENE GLYCOL, CENTELLA ASIATICA EXTRACT, CENTELLA ASIATICA LEAF EXTRACT, SACCHAROMYCES FERMENT, CENTELLA ASIATICA ROOT EXTRACT, HYDROXYPROPYLTRIMONIUM HYALURONATE, ASIATICOSIDE, MADECASSOSIDE, HYDROLYZED HYALURONIC ACID, SODIUM ACETYLATED HYALURONATE, HYALURONIC ACID, SODIUM HYALURONATE CROSSPOLYMER, POTASSIUM HYALURONATE, ASIATIC ACID, MADECASSIC ACID

Other information

Protect the product in this container from excessive heat and direct sun

Questions?

support@us.amorepacific.com

Innisfree Daily UV Defense

Innisfree

DAILY

UV DEFENSE

MINERAL

SUNSCREEN

BROAD SPECTRUM

SPF 45

Color-correcting

Satin Finish

50mL 1.69Fl.Oz.

PACKAGE LABEL

Innisfree

DAILY UV
DEFENSE
MINERAL
SUNSCREEN
BROAD SPECTRUM
SPF 45

COLOR-CORRECTING

SATIN FINISH

10 mL
0.33 Fl. Oz.